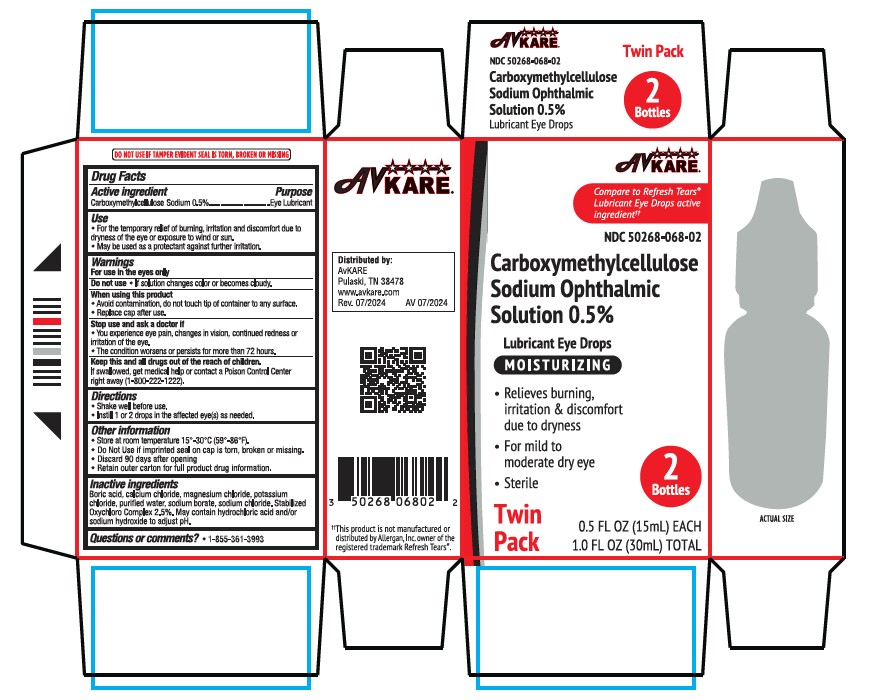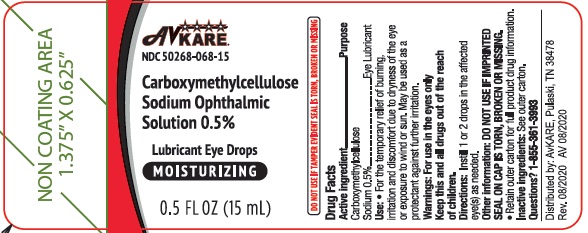 DRUG LABEL: carboxymethylcellulose sodium
NDC: 50268-068 | Form: SOLUTION/ DROPS
Manufacturer: AvPAK
Category: otc | Type: HUMAN OTC DRUG LABEL
Date: 20251111

ACTIVE INGREDIENTS: CARBOXYMETHYLCELLULOSE SODIUM, UNSPECIFIED FORM 5 mg/1 mL
INACTIVE INGREDIENTS: SODIUM CHLORITE; POTASSIUM CHLORIDE; BORIC ACID; CALCIUM CHLORIDE; MAGNESIUM CHLORIDE; WATER; SODIUM BORATE; SODIUM CHLORIDE; HYDROCHLORIC ACID; SODIUM HYDROXIDE; CHLORINE DIOXIDE; SODIUM CHLORATE

Carboxymethylcellulose Sodium Ophthalmic Solution 0.5%
Lubricant Eye Drops

Active ingredient

Carboxymethylcellulose sodium 0.5%

Purpose

Eye lubricant

Uses

- For the temporary relief of burning, irritation, and discomfort due to dryness of the eye or exposure to wind or sun.
- May be used as a protectant against further irritation.

Warnings

- For use in the eyes only

Stop use and ask a doctor if

you experience eye pain, changes in vision, continued redness or irritation of the eye, or if the condition worsens or persists for more than 72 hours.

Keep out of reach of children.

If swallowed, get medical help or contact a Poison Control Center right away.

Directions

Instill 1 or 2 drops in the affected eye(s) as needed.

Other information

- DO NOT USE IF IMPRINTED SEAL ON CAP IS TORN, BROKEN OR MISSING.
- Store at room temperature 15°-30°C (59°-86°F).
- RETAIN OUTER CARTON FOR FULL PRODUCT DRUG INFORMATION.

Inactive ingredients

Boric acid; calcium chloride; magnesium chloride; potassium chloride; purified water; PURITE® (stabilized oxychloro complex); sodium borate; and sodium chloride. May also contain hydrochloric acid and/or sodium hydroxide to adjust pH.

Questions or comments?

1-855-361-3993